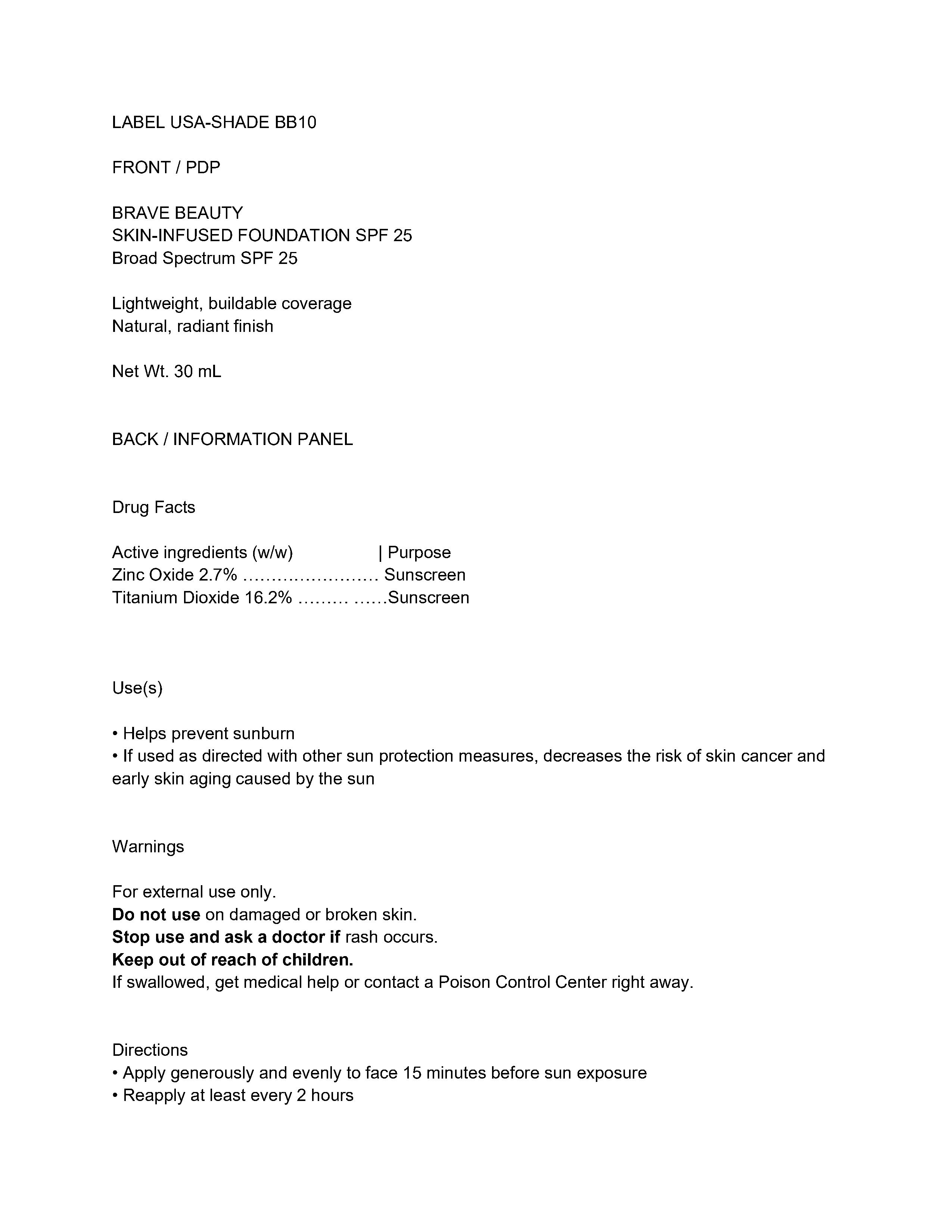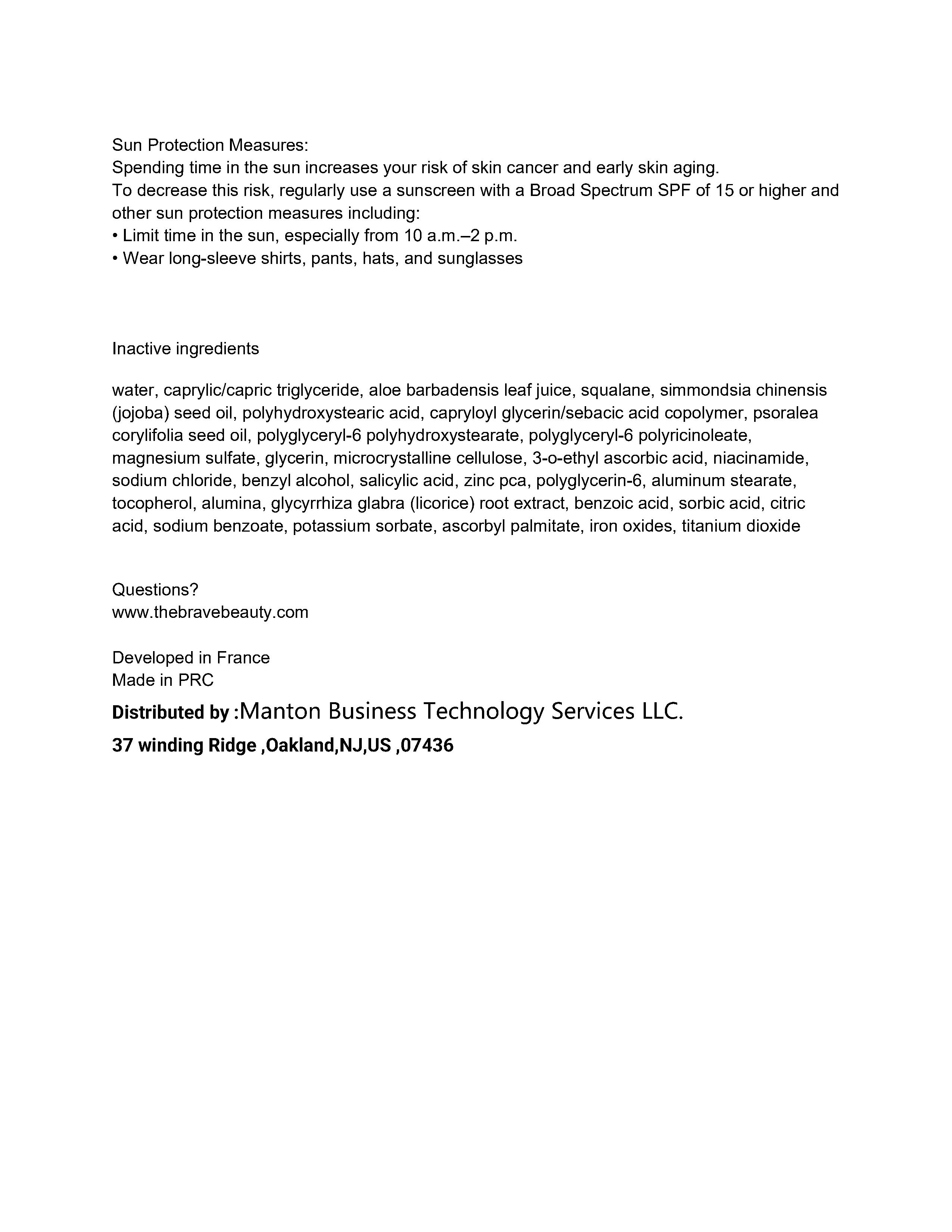 DRUG LABEL: SKIN-INFUSED FOUNDATION SPF 25- shade BB10
NDC: 82953-060 | Form: CREAM
Manufacturer: Cosmuses Cosmetics (Ningbo) Co., Ltd.
Category: otc | Type: HUMAN OTC DRUG LABEL
Date: 20260206

ACTIVE INGREDIENTS: ZINC OXIDE 2.7 g/100 mL; TITANIUM DIOXIDE 16.2 g/100 mL
INACTIVE INGREDIENTS: MAGNESIUM SULFITE; MICROCRYSTALLINE CELLULOSE; NIACINAMIDE; TOCOPHEROL; CITRIC ACID; WATER; ALOE BARBADENSIS LEAF JUICE; POLYGLYCERIN-6; POLYHYDROXYSTEARIC ACID (2300 MW); CAPRYLIC/CAPRIC TRIGLYCERIDE; SODIUM CHLORIDE; POLYGLYCERYL-6 POLYRICINOLEATE; ALUMINUM STEARATE; ALUMINA; GLYCYRRHIZA GLABRA (LICORICE) ROOT; POTASSIUM SORBATE; FERRIC OXIDE RED; GLYCERIN; SORBIC ACID; SIMMONDSIA CHINENSIS (JOJOBA) SEED OIL; ZINC PCA; 3-O-ETHYL ASCORBIC ACID; CULLEN CORYLIFOLIUM FRUIT; ASCORBYL PALMITATE; CAPRYLOYL GLYCERIN/SEBACIC ACID COPOLYMER (2000 MPA.S); SALICYLIC ACID; SODIUM BENZOATE; SQUALANE; POLYGLYCERYL-6 STEARATE; BENZYL ALCOHOL; BENZOIC ACID

BRAVE BEAUTY
SKIN-INFUSED FOUNDATION SPF 25
Broad Spectrum SPF 25- Shade BB10

Drug Facts

Active ingredients

Zinc oxide 2.7%

Titanium Dioxide 16.2%

Purpose

Sunscreen

Uses

- Helps prevent sunburn
- If used as directed with other sun protection measures, decreases the risk of skin cancer and early skin aging caused by the sun

WARNINGS

For external use only.

Do not use on damaged or broken skin.

Stop use and ask a doctor: if rash occurs.

Keep out of reach of children. If swallowed, get medical help or contact a Poison Control Center right away.

Directions

• Apply generously and evenly to face 15 minutes before sun exposure

• Reapply at least every 2 hours

Sun Protection Measures:

Spending time in the sun increases your risk of skin cancer and early skin aging.

To decrease this risk, regularly use a sunscreen with a Broad Spectrum SPF of 15 or higher and other sun protection measures including:

• Limit time in the sun, especially from 10 a.m.–2 p.m.

• Wear long-sleeve shirts, pants, hats, and sunglasses

Inactive ingredients

water, caprylic/capric triglyceride, aloe barbadensis leaf juice, squalane, simmondsia chinensis (jojoba) seed oil, polyhydroxystearic acid, capryloyl glycerin/sebacic acid copolymer, psoralea corylifolia seed oil, polyglyceryl-6 polyhydroxystearate, polyglyceryl-6 polyricinoleate, magnesium sulfate, glycerin, microcrystalline cellulose, 3-o-ethyl ascorbic acid, niacinamide, sodium chloride, benzyl alcohol, salicylic acid, zinc pca, polyglycerin-6, aluminum stearate, tocopherol, alumina, glycyrrhiza glabra (licorice) root extract, benzoic acid, sorbic acid, citric acid, sodium benzoate, potassium sorbate, ascorbyl palmitate, iron oxides, titanium dioxide

Questions or comments?

www.thebravebeauty.com

Distributed by Manton Business Technology Services LLC.

37 winding Ridge ,Oakland,NJ,US ,07436